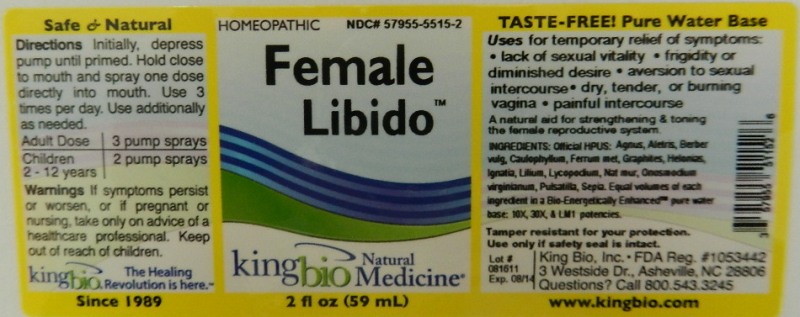 DRUG LABEL: Female Libido
NDC: 57955-5515 | Form: LIQUID
Manufacturer: King Bio Inc.
Category: homeopathic | Type: HUMAN OTC DRUG LABEL
Date: 20111130

ACTIVE INGREDIENTS: CHASTE TREE 10 [hp_X]/59 mL; ALETRIS FARINOSA ROOT 10 [hp_X]/59 mL; BERBERIS VULGARIS ROOT BARK 10 [hp_X]/59 mL; CAULOPHYLLUM THALICTROIDES ROOT 10 [hp_X]/59 mL; IRON 10 [hp_X]/59 mL; GRAPHITE 10 [hp_X]/59 mL; CHAMAELIRIUM LUTEUM ROOT 10 [hp_X]/59 mL; STRYCHNOS IGNATII SEED 10 [hp_X]/59 mL; LILIUM LANCIFOLIUM WHOLE FLOWERING 10 [hp_X]/59 mL; LYCOPODIUM CLAVATUM SPORE 10 [hp_X]/59 mL; SODIUM CHLORIDE 10 [hp_X]/59 mL; ONOSMODIUM VIRGINIANUM WHOLE 10 [hp_X]/59 mL; PULSATILLA VULGARIS 10 [hp_X]/59 mL; SEPIA OFFICINALIS JUICE 10 [hp_X]/59 mL
INACTIVE INGREDIENTS: WATER

Female Libido

Active ingredients

Official HPUS: Agnus Castus, Aletris Farinosa, Berberis Vulgaris, Caulophyllum Thalictroides, Ferrum Metallicum, Graphites, Helonias Dioica, Ignatia Amara, Lilium Tigrinum, Lycopodium Clavatum, Natrum Muriaticum, Onosmodium Virginianum, Pulsatilla, Sepia.

Reference image female libido.jpg

Inactive Ingredient

Equal volumes of each ingredient in a Bio-Energetically Enhanced pure water base: 10X, 30X, LM1 potencies.

Reference image female libido.jpg

Purpose

Uses for temporary relief of symptoms: lack of sexual vitality, frigidity or diminished desire, aversion to sexual intercourse, dry, tender, or burning vagina,painful intercourse.

A natural aid for strengthening and toning the female reproductive system.

Reference image female libido.jpg

Directions

Initially, depress pump until primed. Hold close to mouth and spray one dose directly into mouth. Use 3 times per day. Use additionally as needed.

Adult Dose 3 pump sprays

Children (2-12 years) 2 pump sprays

Reference image female libido.jpg

Warnings

If symptoms persist or worsen, or if pregnant or nursing, take only on advice of a healthcare professional. Keep out of reach of children.

Tamper resistant for your protection. Use only if safety seal is intact.

Reference image female libido.jpg

Keep out of reach of children.

Reference image female libido.jpg

Indications and Usage

Uses for temporary relief of symptoms:

- lack of sexual vitality
- frigidity or diminished desire
- aversion to sexual intercourse
- dry, tender, or burning vagina
- painful intercourse

A natural aid for strengthening and toning the female reproductive system.
Reference image female libido.jpg

PACKAGE LABEL

King Bio, Inc.

3 Westside Drive,

Asheville, NC 28806

Questions? Call 800.543.3245

www.kingbio.com